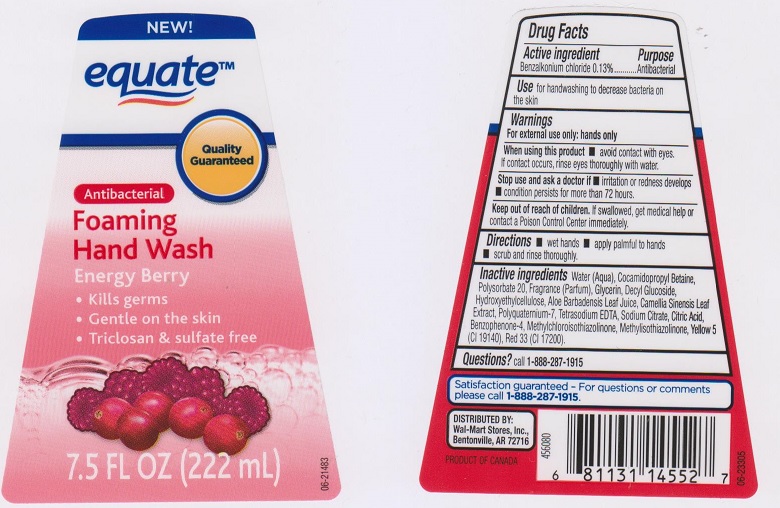 DRUG LABEL: Equate Foaming Hand Wash
NDC: 49035-036 | Form: SOAP
Manufacturer: Wal-Mart Stores Inc
Category: otc | Type: HUMAN OTC DRUG LABEL
Date: 20170428

ACTIVE INGREDIENTS: BENZALKONIUM CHLORIDE 1.3 mg/1 mL
INACTIVE INGREDIENTS: WATER; COCAMIDOPROPYL BETAINE; POLYSORBATE 20; GLYCERIN; DECYL GLUCOSIDE; HYDROXYETHYL CELLULOSE (5000 CPS AT 1%); ALOE VERA LEAF; GREEN TEA LEAF; POLYQUATERNIUM-7 (70/30 ACRYLAMIDE/DADMAC; 1600000 MW); EDETATE SODIUM; SODIUM CITRATE; CITRIC ACID MONOHYDRATE; SULISOBENZONE; METHYLCHLOROISOTHIAZOLINONE; METHYLISOTHIAZOLINONE; FD&C YELLOW NO. 5; D&C RED NO. 33

Active ingredient

Benzalkonium Chloride 0.13%

Purpose

Antibacterial

Use

for handwashing to decrease bacteria on the skin.

Warnings

For external use only; hands only

When using this product

- avoid contact with eyes. If contact occurs, rinse eyes thoroughly with water.

Stop use and ask a doctor if

- irritation or redness develops
- condition persists for more than 72 hours

Keep out of reach of children.

If swallowed, get medical help or contact a Poison Control Center immediately.

Directions

- wet hands
- apply palmful to hands
- scrub and rinse thoroughly.

Inactive ingredients

Water (Aqua), Cocamidopropyl Betaine, Polysorbate 20, Fragrance (Parfum), Glycerin, Decyl Glucoside, Hydroxyethylcellulose, Aloe Barbadensis Leaf Juice, Camellia Sinensis Leaf Extract, Polyquaternium-7, Tetrasodium EDTA, Sodium Citrate, Citric Acid, Benzophenone-4, Methylchloroisothiazolinone, Methylisothiazolinone, Yellow 5 (CI 19140), Red 33 (CI 17200).

Questions?

call 1-888-287-1915